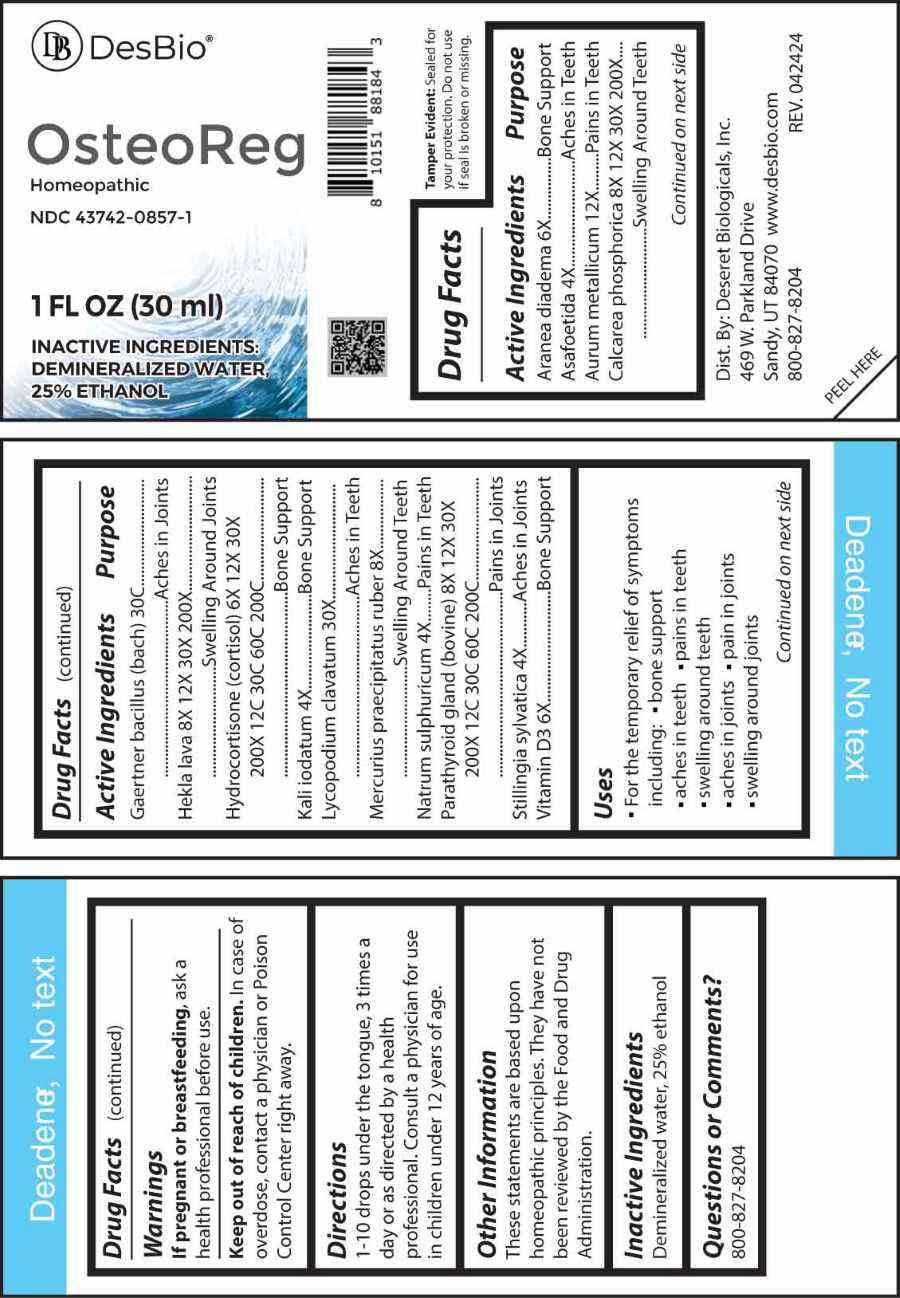 DRUG LABEL: Osteoreg
NDC: 43742-0857 | Form: LIQUID
Manufacturer: Deseret Biologicals, Inc.
Category: homeopathic | Type: HUMAN OTC DRUG LABEL
Date: 20240814

ACTIVE INGREDIENTS: FERULA ASSA-FOETIDA RESIN 4 [hp_X]/1 mL; POTASSIUM IODIDE 4 [hp_X]/1 mL; SODIUM SULFATE 4 [hp_X]/1 mL; STILLINGIA SYLVATICA ROOT 4 [hp_X]/1 mL; ARANEUS DIADEMATUS 6 [hp_X]/1 mL; CHOLECALCIFEROL 6 [hp_X]/1 mL; HYDROCORTISONE 6 [hp_X]/1 mL; MERCURIC OXIDE 8 [hp_X]/1 mL; TRIBASIC CALCIUM PHOSPHATE 8 [hp_X]/1 mL; HEKLA LAVA 8 [hp_X]/1 mL; BOS TAURUS PARATHYROID GLAND 8 [hp_X]/1 mL; GOLD 12 [hp_X]/1 mL; LYCOPODIUM CLAVATUM SPORE 30 [hp_X]/1 mL; SALMONELLA ENTERICA SUBSP. ENTERICA SEROVAR ENTERITIDIS 30 [hp_C]/1 mL
INACTIVE INGREDIENTS: WATER; ALCOHOL

DRUG FACTS:

ACTIVE INGREDIENTS:

Aranea Diadema 6X, Asafoetida 4X, Aurum Metallicum 12X, Calcarea Phosphorica 8X, 12X, 30X, 200X, Gaertner Bacillus (Bach) 30C, Hekla Lava 8X, 12X, 30X, 200X, Hydrocortisone (Cortisol) 6X, 12X, 30X, 200X, 12C, 30C, 60C, 200C, Kali Iodatum 4X, Lycopodium Clavatum 30X, Mercurius Praecipitatus Ruber 8X, Natrum Sulphuricum 4X, Parathyroid Gland (Bovine) 8X, 12X, 30X, 200X, 12C, 30C, 60C, 200C, Stillingia Sylvatica 4X, Vitamin D3 6X.

PURPOSE:

Aranea Diadema – Bone Support, Asafoetida – Aches in Teeth, Aurum Metallicum – Pains in Teeth, Calcarea Phosphorica – Swelling Around Teeth, Gaertner Bacillus (Bach) – Aches in Joints, Hekla Lava – Swelling Around Joints, Hydrocortisone (Cortisol) – Bone Support, Kali Iodatum – Bone Support, Lycopodium Clavatum – Aches in Teeth, Mercurius Praecipitatus Ruber – Swelling Around Teeth, Natrum Sulphuricum – Pains in Teeth, Parathyroid Gland (Bovine) – Pains in Joints, Stillingia Sylvatica – Aches in Joints, Vitamin D3 – Bone Support

USES:

• For the temporary relief of symptoms including:

• bone support • aches in teeth • pains in teeth

• swelling around teeth • aches in joints

• Pain in joints • Swelling around joints

These statements are based upon homeopathic principles. They have not been reviewed by the Food and Drug Administration.

WARNINGS:

If pregnant or breast-feeding, ask a health professional before use.

Keep out of reach of children. In case of overdose, contact a physician or Poison Control Center right away.

Tamper Evident: Sealed for your protection. Do not use if seal is broken or missing.

KEEP OUT OF REACH OF CHILDREN:

In case of overdose, contact a physician or Poison Control Center right away.

DIRECTIONS:

1-10 drops under the tongue, 3 times a day or as directed by a health professional. Consult a physician for use in children under 12 years of age.

INACTIVE INGREDIENTS:

Demineralized water, 25% ethanol

QUESTIONS:

Dist. By: Deseret Biologicals, Inc.

469 W. Parkland Drive

Sandy, UT 84070

www.desbio.com

800-827-8204

PACKAGE LABEL DISPLAY:

Des Bio

OsteoReg

Homeopathic

NDC 43742-0857-1

1 FL OZ (30 ml)